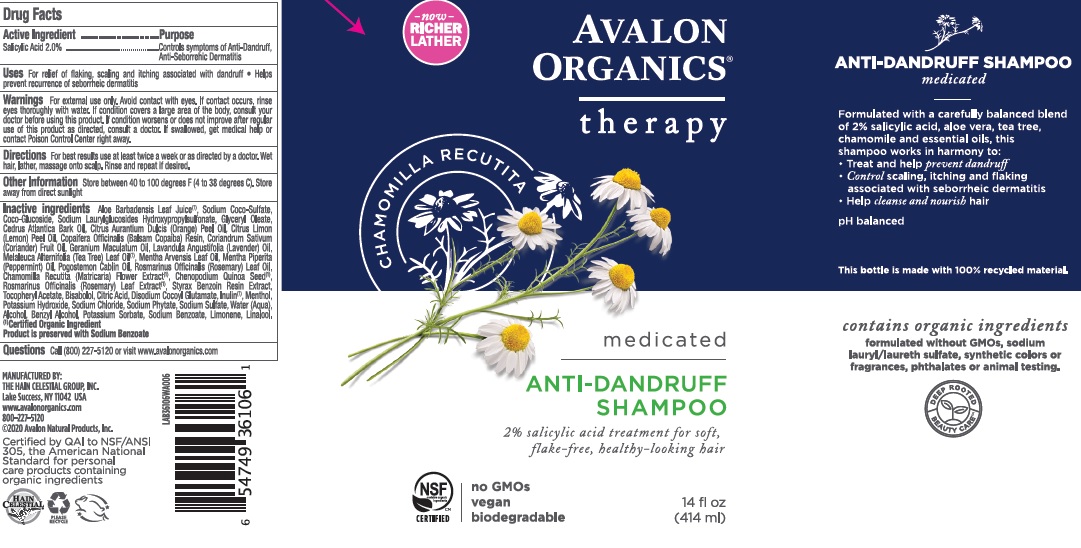 DRUG LABEL: Avalon Organics Antidandruff
NDC: 61995-1606 | Form: SHAMPOO
Manufacturer: The Hain Celestial Group, Inc.
Category: otc | Type: HUMAN OTC DRUG LABEL
Date: 20250711

ACTIVE INGREDIENTS: SALICYLIC ACID 2 g/414 g
INACTIVE INGREDIENTS: GERANIUM MACULATUM ROOT OIL; GLYCERYL OLEATE; LIMONENE, (+/-)-; SODIUM COCO-SULFATE; DISODIUM COCOYL GLUTAMATE; LINALOOL, (+/-)-; COCO GLUCOSIDE; SODIUM SULFATE; ALOE VERA LEAF; WATER; CHAMOMILE; MELALEUCA ALTERNIFOLIA LEAF; ROSMARINUS OFFICINALIS FLOWER; STYRAX BENZOIN RESIN; CEDRUS ATLANTICA BARK OIL; ORANGE OIL; LEMON OIL; COPAIFERA OFFICINALIS RESIN; CORIANDER OIL; LAVENDER OIL; MENTHA ARVENSIS LEAF OIL; MENTHA PIPERITA; POGOSTEMON CABLIN WHOLE; ROSEMARY OIL; .ALPHA.-BISABOLOL, (+)-; INULIN; MENTHOL; POTASSIUM HYDROXIDE; .ALPHA.-TOCOPHEROL ACETATE; ALCOHOL; BENZYL ALCOHOL; POTASSIUM SORBATE; SODIUM BENZOATE; CHENOPODIUM QUINOA SEED; SODIUM CHLORIDE; ANHYDROUS CITRIC ACID; LAURYL GLUCOSIDE; HEXASODIUM PHYTATE

Avalon Organic Anti-dandruff Shampoo
153-067C, F01866
Items: AV36106 414g, AV35009 325ml

WARNINGS

For external use only. Avoid contact with eyes. Rinse eyes throughly with water in case contact ossurs. Discontinue to use and contact your physician if irritation develops.

ACTIVE INGREDIENT

Salicylic Acid 2.0%

PURPOSE

Controls symptoms of dandruff, seboric dermatitis and psoriasis

Keep out of reach of children. If swallowed, get medical help or contact Poison Control Center right away.

INDICATIONS AND USAGE

For relief of flaking, scaling and itching associated with dandruff. Helps prevent seborrheic dermatitis

DOSAGE AND ADMINISTRATION

For the best results use at least three times each week. Wet hair, lather, massage onto scalp. Rinse and repeat if desired.

INACTIVE INGREDIENT

Aloe Barbadensis Leaf Juice (1), Sodium Coco-Sulfate, Coco-Glucoside, Sodium Laurylglucosides Hydroxypropylsulfonate, Glyceryl Oleate, Cedrus Atlantica Bark Oil, Citrus Aurantium Dulcis (Orange) Peel Oil, Citrus Limon (Lemon) Peel Oil, Copaifera Officinalis (Balsam Copaiba) Resin, Coriandrum Sativum (Coriander) Fruit Oil, Geranium Maculatum Oil, Lavandula Angustifolia (Lavender) Oil, Melaleuca Alternifolia (Tea Tree) Leaf Oil (1), Mentha Arvensis Leaf Oil, Mentha Piperita (Peppermint) Oil, Pogostemon Cablin Oil, Rosmarinus Officinalis (Rosemary) Leaf Oil, Chamomilla Recutita (Matricaria) Flower Extract (1), Chenopodium Quinoa Seed (1), Rosmarinus Officinalis (Rosemary) Leaf Extract (1), Styrax Benzoin Resin Extract, Tocopheryl Acetate, Bisabolol, Citric Acid, Disodium Cocoyl Glutamate, Inulin (1), Menthol, Potassium Hydroxide, Sodium Chloride, Sodium Phytate, Sodium Sulfate, Water (Aqua), Alcohol, Benzyl Alcohol, Potassium Sorbate, Sodium Benzoate, Limonene, Linalool.

(1) Certified Organic Ingredient